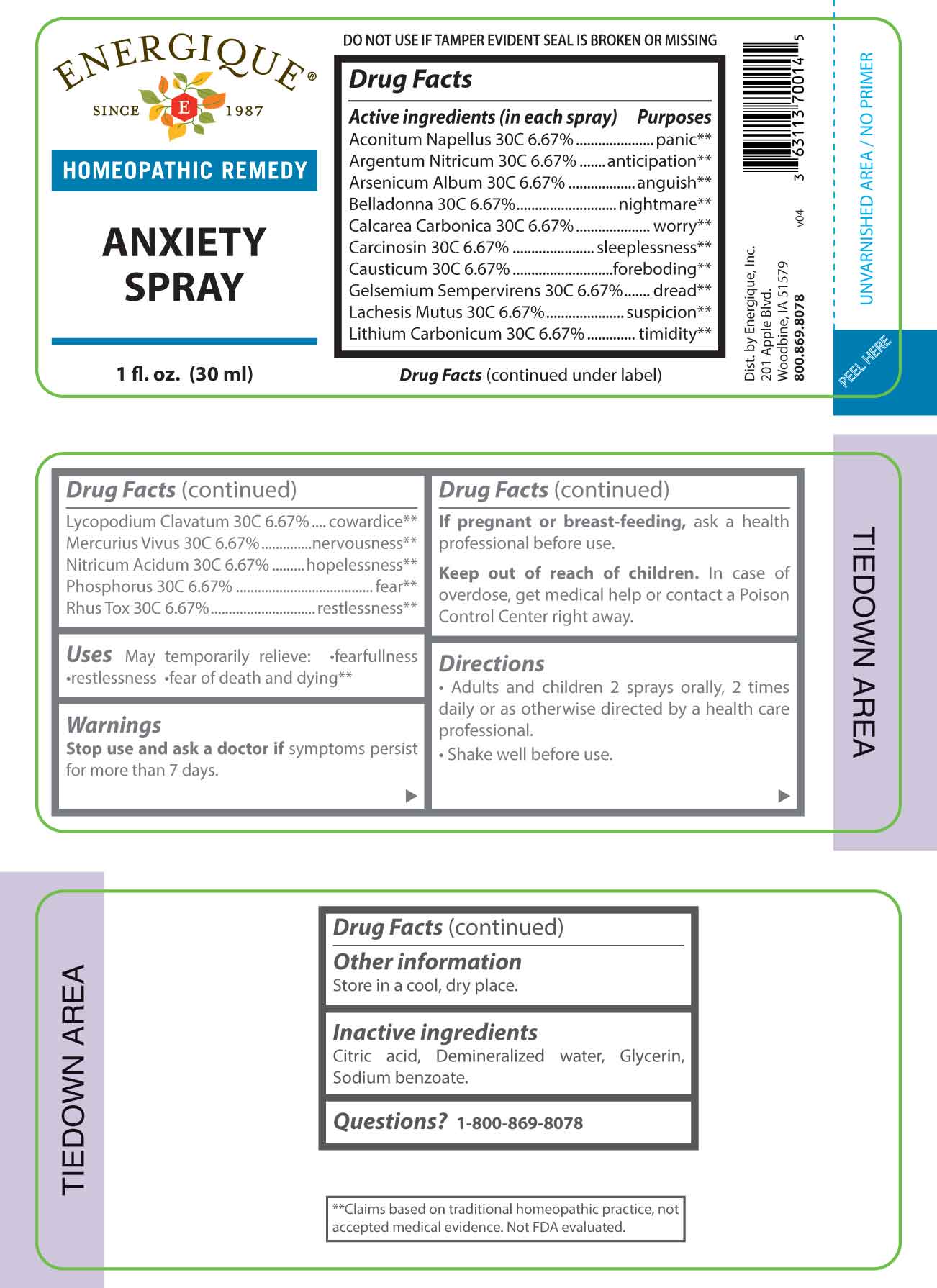 DRUG LABEL: Anxiety
NDC: 44911-0685 | Form: SPRAY
Manufacturer: Energique, Inc.
Category: homeopathic | Type: HUMAN OTC DRUG LABEL
Date: 20231103

ACTIVE INGREDIENTS: ACONITUM NAPELLUS WHOLE 30 [hp_C]/1 mL; SILVER NITRATE 30 [hp_C]/1 mL; ARSENIC TRIOXIDE 30 [hp_C]/1 mL; ATROPA BELLADONNA 30 [hp_C]/1 mL; OYSTER SHELL CALCIUM CARBONATE, CRUDE 30 [hp_C]/1 mL; HUMAN BREAST TUMOR CELL 30 [hp_C]/1 mL; CAUSTICUM 30 [hp_C]/1 mL; GELSEMIUM SEMPERVIRENS ROOT 30 [hp_C]/1 mL; LACHESIS MUTA VENOM 30 [hp_C]/1 mL; LITHIUM CARBONATE 30 [hp_C]/1 mL; LYCOPODIUM CLAVATUM SPORE 30 [hp_C]/1 mL; MERCURY 30 [hp_C]/1 mL; NITRIC ACID 30 [hp_C]/1 mL; PHOSPHORUS 30 [hp_C]/1 mL; TOXICODENDRON PUBESCENS LEAF 30 [kp_C]/1 mL
INACTIVE INGREDIENTS: ANHYDROUS CITRIC ACID; GLYCERIN; SODIUM BENZOATE

DRUG FACTS:

ACTIVE INGREDIENTS:

Aconitum Napellus 30C 6.67%, Argentum Nitricum 30C 6.67% , Arsenicum Album 30C 6.67%, Belladonna 30C 6.67%, Calcarea Carbonica 30C 6.67%, Carcinosin 30C 6.67%, Causticum 30C 6.67%, Gelsemium Sempervirens 30C 6.67%, Lachesis Mutus 30C 6.67%, Lithium Carbonicum 30C 6.67%, Lycopodium Clavatum 30C 6.67%, Mercurius Vivus 30C 6.67%, Nitricum Acidum 30C 6.67%, Phosphorus 30C 6.67%, Rhus Tox 30C 6.67%.

PURPOSE:

Aconitum Napellus - panic,** Argentum Nitricum - anticipation,** Arsenicum Album - anguish,** Belladonna - nightmare,** Calcarea Carbonica - worry,** Carcinosin - sleeplessness,** Causticum - foreboding,** Gelsemium Sempervirens - dread,** Lachesis Mutus - suspicion,** Lithium Carbonicum - timidity,** Lycopodium Clavatum - cowardice,** Mercurius Vivus - nervousness,** Nitricum Acidum - hopelessness,** Phosphorus - fear,** Rhus Tox - restlessness.**

**Claims based on traditional homeopathic practice, not accepted medical evidence. Not FDA evaluated.

USES:

May temporarily relieve: • fearfullness • restlessness • fear of death and dying**

**Claims based on traditional homeopathic practice, not accepted medical evidence. Not FDA evaluated.

WARNINGS:

Stop use and ask a doctor if symptoms persist for more than 7 days.

If pregnant or breast-feeding, ask a health professional before use.

Keep out of reach of children. In case of overdose, get medical help or contact a Poison Control Center right away.

DO NOT USE IF TAMPER EVIDENT SEAL IS BROKEN OR MISSING

Store in a cool, dry place.

KEEP OUT OF REACH OF CHILDREN:

In case of overdose, get medical help or contact a Poison Control Center right away.

DIRECTIONS:

• Adults and children 2 sprays orally, 2 times daily or as otherwise directed by a health care professional. Shake well before use.

INACTIVE INGREDIENTS:

Citric acid, Demineralized water, Glycerin, Sodium benzoate.

QUESTIONS:

Dist. by Energique, Inc.

201 Apple Blvd.

Woodbine, IA 51579

800.869.8078

PACKAGE LABEL DISPLAY:

ENERGIQUE

SINCE 1987

HOMEOPATHIC REMEDY

ANXIETY SPRAY

1 fl. oz. (30 ml)